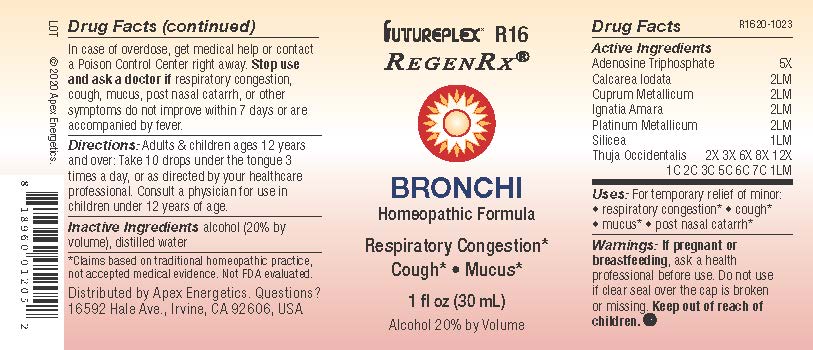 DRUG LABEL: R16
NDC: 63479-1816 | Form: SOLUTION/ DROPS
Manufacturer: Apex Energetics Inc.
Category: homeopathic | Type: HUMAN OTC DRUG LABEL
Date: 20240108

ACTIVE INGREDIENTS: ADENOSINE TRIPHOSPHATE 5 [hp_X]/1 mL; COPPER 2 [hp_Q]/1 mL; STRYCHNOS IGNATII SEED 2 [hp_Q]/1 mL; PLATINUM 2 [hp_Q]/1 mL; SILICON DIOXIDE 1 [hp_Q]/1 mL; CALCIUM IODIDE 2 [hp_Q]/1 mL; THUJA OCCIDENTALIS LEAFY TWIG 1 [hp_Q]/1 mL
INACTIVE INGREDIENTS: ALCOHOL; WATER

R16

Active Ingredients
Adenosine Triphosphate | 5X
Calcarea Iodata | 2LM
Cuprum Metallicum | 2LM
Ignatia Amara | 2LM
Platinum Metallicum | 2LM
Silicea | 1LM
Thuja Occidentalis | 2X 3X 6X 8X 12X 1C 2C 3C 5C 6C 7C 1LM

INDICATIONS AND USAGE

Uses:

For temporary relief of minor:

respiratory congestion*

cough*

mucus*

post nasal catarrh*

*Claims based on traditional homeopathic practice, not accepted medical evidence. Not FDA evaluated.

Warnings:

PREGNANCY OR BREAST FEEDING

If pregnant or breastfeeding, ask a health professional before use.

Do not use if clear seal over the cap is broken or missing.

Keep out of reach of children. In case of overdose, get medical help or contact a Poison Control Center right away.

Stop use and ask a doctor if respiratory congestion, cough, mucus, post nasal catarrh, or other symptoms do not improve within 7 days or are accompanied by fever.

Directions:

Adults & children ages 12 years and over: Take 10 drops under the tongue 3 times a day, or as directed by your healthcare professional. Consult a physician for use in children under 12 years of age.

Inactive Ingredients

alcohol (20% by volume), distilled water

Distributed by Apex Energetics. Questions?

16592 Hale Ave., Irvine, CA 92606, USA

PACKAGE LABEL

FUTUREPLEX® R16

REGENRX®

BRONCHI

Homeopathic Formula

Respiratory Congestion*

Cough* Mucus*

1 fl oz (30 mL)

Alcohol 20% by Volume